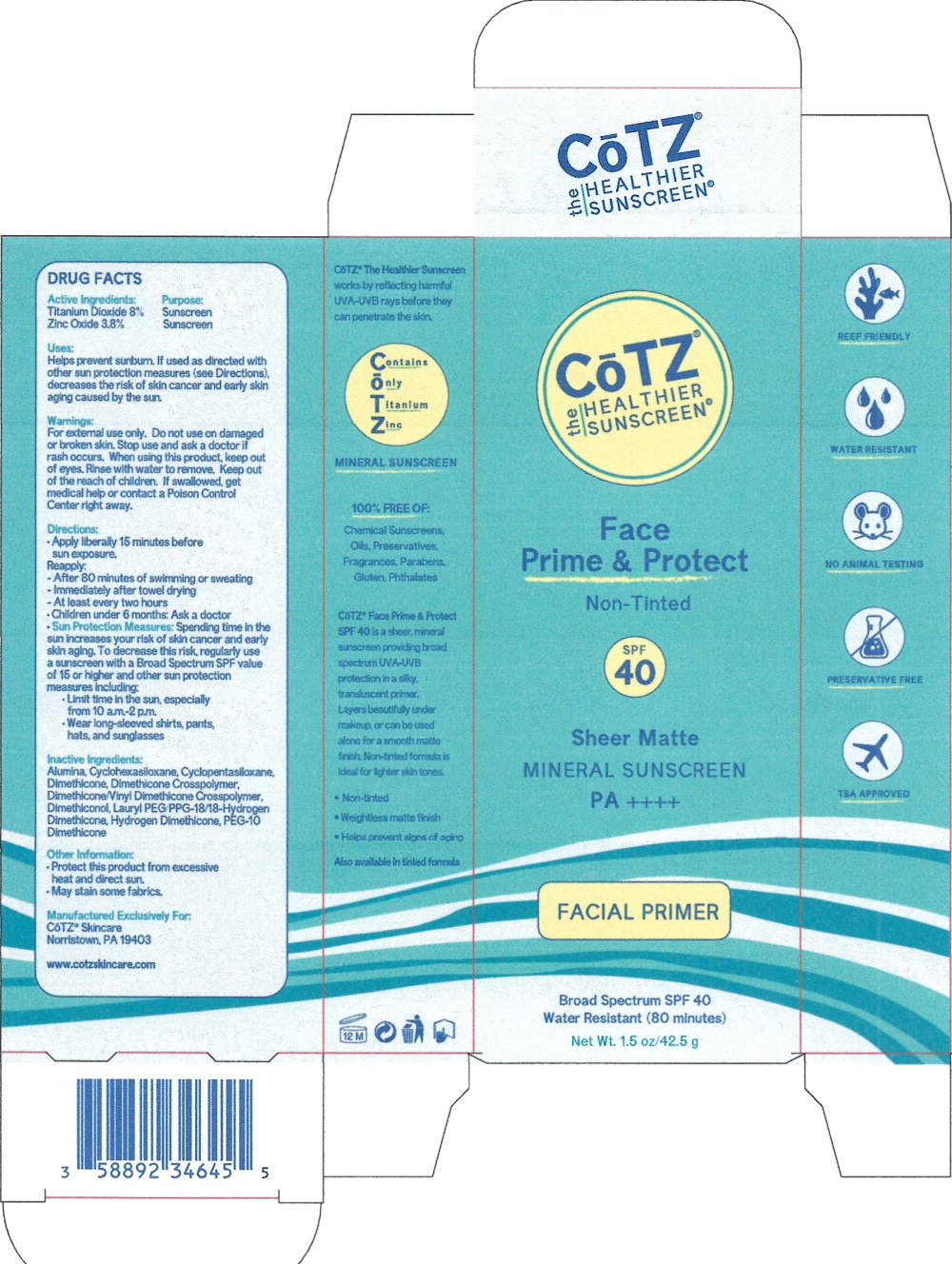 DRUG LABEL: CoTZ Face Prime and Protect SPF 40 (Non-Tinted)
NDC: 58892-348 | Form: CREAM
Manufacturer: Fallien Cosmeceuticals, LTD
Category: otc | Type: HUMAN OTC DRUG LABEL
Date: 20250109

ACTIVE INGREDIENTS: Titanium Dioxide 80 mg/1 g; Zinc Oxide 38 mg/1 g
INACTIVE INGREDIENTS: Aluminum Hydroxide; Cyclomethicone 6; Cyclomethicone 5; Dimethicone 20; Dimethicone Crosspolymer (450000 MPA.S AT 12% in Cyclopentasiloxane); Dimethicone/Vinyl Dimethicone Crosspolymer (Soft Particle); Dimethiconol (2000 CST); Lauryl PEG/PPG-18/18 Methicone; Hydrogen Dimethicone (20 CST); PEG-10 Dimethicone (600 CST)

DRUG FACTS

Active Ingredients:

Titanium Dioxide 8%

Zinc Oxide 3.8%

Purpose:

Sunscreen

Sunscreen

Uses:

Helps prevent sunburn. If used as directed with other sun protection measures (see Directions), decreases the risk of skin cancer and early skin aging caused by the sun.

Warnings:

KEEP OUT OF REACH OF CHILDREN

For external use only. Do not use on damaged or broken skin. Stop use and ask a doctor if rash occurs. When using this product, keep out of eyes. Rinse with water to remove. Keep out of the reach of children. If swallowed, get medical help or contact a Poison Control Center right away.

Directions:

- Apply liberally 15 minutes before sun exposure.

Reapply:

- After 80 minutes of swimming or sweating
- Immediately after towel drying
- At least every two hours

- Children under 6 months: Ask a doctor
- Sun Protection Measures: Spending time in the sun increases your risk of skin cancer and early skin aging. To decrease this risk, regularly use a sunscreen with a Broad Spectrum SPF value of 15 or higher and other sun protection measures including:
  - Limit time in the sun, especially from 10 a.m.-2 p.m.
  - Wear long-sleeved shirts, pants, hats, and sunglasses

Inactive Ingredients:

Alumina, Cyclohexasiloxane, Cyclopentasiloxane, Dimethicone. Dimethicone Crosspolymer. Dimethicone/Vinyl Dimethicone Crosspolymer, Dimethiconol, Lauryl PEG/PPG-18/18-Hydrogen Dimethicone, Hydrogen Dimethicone, PEG-10 Dimethicone

Other Information:

- Protect this product from excessive heat and direct sun.
- May stain some fabrics.

Manufactured Exclusively For:
CoTZ® Skincare
Norristown. PA 19403

www.cotzskincare.com

Principal Display Panel – 42.5 g Carton Label

CoTZ®

the HEALTHIER
SUNSCREEN®

Face
Prime & Protect

Non-Tinted

SPF
40

Sheer Matte

MINERAL SUNSCREEN

PA ++++

FACIAL PRIMER

Broad Spectrum SPF 40
Water Resistant (80 minutes)

Net Wt. 1.5 oz/42.5 g